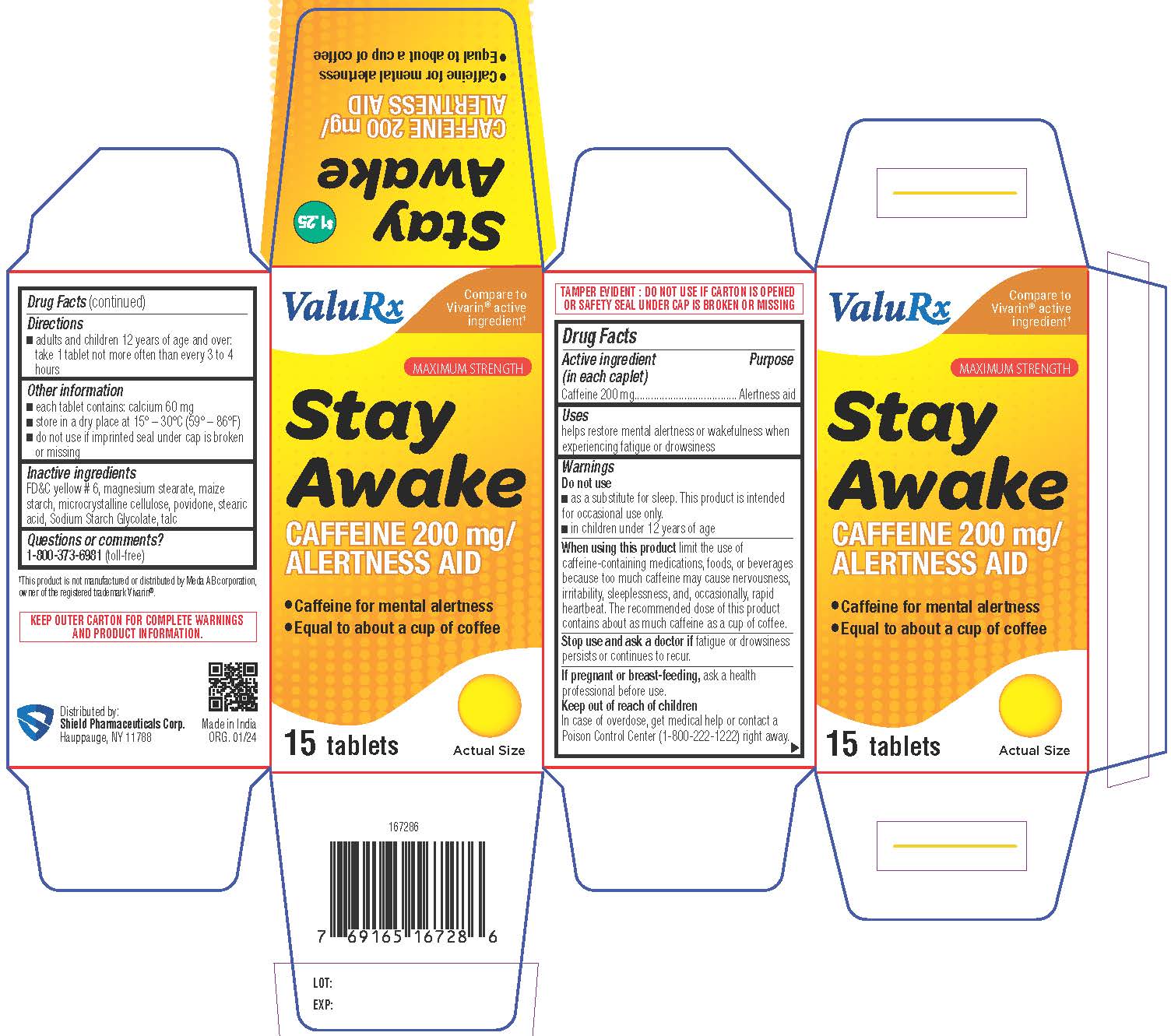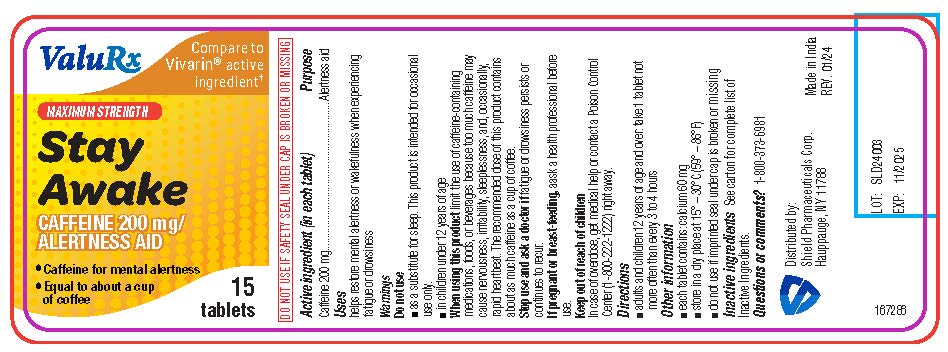 DRUG LABEL: Stay Awake
NDC: 83059-0008 | Form: TABLET, COATED
Manufacturer: Shield Pharmaceuticals Corp
Category: otc | Type: HUMAN OTC DRUG LABEL
Date: 20251209

ACTIVE INGREDIENTS: CAFFEINE 200 mg/1 1
INACTIVE INGREDIENTS: FD&C YELLOW NO. 6; MAGNESIUM STEARATE; STARCH, POTATO; MICROCRYSTALLINE CELLULOSE; POVIDONE; STEARIC ACID; SODIUM STARCH GLYCOLATE TYPE A; TALC

Stay Awake

Drug Facts

Active ingredient (in each liquid-filled capsule)

Caffeine 200 mg

Purpose

Alertness aid

Uses

helps restore mental alertness or wakefulness when experiencing fatigue or drowsiness

Do not use

- as a substitute for sleep. This product is intended for occasional use only.
- in children under 12 years of age

WHEN USING

When using this productlimit the use of caffeine-containing medications, foods, or beverages because too much caffeine may cause nervousness, irritability, sleeplessness, and, occasionally, rapid heartbeat. The recommended dose of this product contains about as much caffeine as a cup of coffee.

Stop use and ask a doctorif fatigue or drowsiness persists or continues to recur.

PREGNANCY OR BREAST FEEDING

If pregnant or breast-feeding,ask a health professional before use.

Keep out of reach of children. In case of overdose, get medical help or contact a Poison Control Center (1-800-222-1222) right away.

Directions

adults and children 12 years and over:

- take 1 tablet not more often than every 3 to 4 hours

Other information

- each tablet contains: calcium 60 mg
- store in a dry place at 15° – 30°C (59° – 86°F)
- do not use if imprinted seal under cap is broken or missing

Questions or comments?

1-800-373-6981 (toll-free)

Inactive ingredients

FD&C yellow # 6, magnesium stearate, maize starch, microcrystalline cellulose, povidone, stearic acid, Sodium Starch Glycolate, talc

Distributed by:
Shield Pharmaceuticals Corp.
Ronkonkoma, NY 11779

PRINCIPAL DISPLAY PANEL

Stay Awake

Caffeine 200 mg/ Alertness Aid

- Caffeine for mental alertness
- Equal to about a cup of coffee

Carton

Label